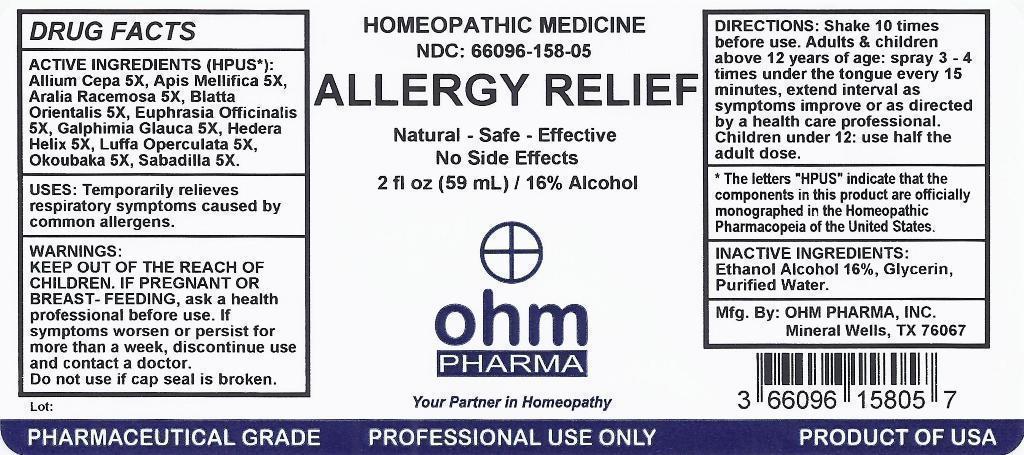 DRUG LABEL: ALLERGY RELIEF
                
NDC: 66096-158 | Form: SPRAY
Manufacturer: OHM PHARMA INC.
Category: homeopathic | Type: HUMAN OTC DRUG LABEL
Date: 20150421

ACTIVE INGREDIENTS: ONION 5 [hp_X]/1 mL; APIS MELLIFERA 5 [hp_X]/1 mL; ARALIA RACEMOSA ROOT 5 [hp_X]/1 mL; BLATTA ORIENTALIS 5 [hp_X]/1 mL; EUPHRASIA STRICTA 5 [hp_X]/1 mL; GALPHIMIA GLAUCA FLOWERING TOP 5 [hp_X]/1 mL; HEDERA HELIX FLOWERING TWIG 5 [hp_X]/1 mL; LUFFA OPERCULATA FRUIT 5 [hp_X]/1 mL; OKOUBAKA AUBREVILLEI BARK 5 [hp_X]/1 mL; SCHOENOCAULON OFFICINALE SEED 5 [hp_X]/1 mL
INACTIVE INGREDIENTS: ALCOHOL; GLYCERIN; WATER

ALLERGY RELIEF

ACTIVE INGREDIENTS (HPUS*):

Allium Cepa 5X, Apis Mellifica 5X, Aralia Racemosa 5X, Euphrasia Officinalis 5X, Galphimia Glauca 5X, Hedera Helix 5X, Luffa Operculata 5X, Okoubaka 5X, Sabadilla 5X.

ACTIVE INGREDIENT

* The letters "HPUS" indicate that the components in this product are officially monographed in the Homeopathic Pharmacopeia of the United States.

INDICATIONS AND USAGE

USES: Temporarily relieves respiratory symptoms caused by common allergens.

WARNINGS:

If pregnant or breast-feeding, ask a health professional before use. If symptoms persist for more than a week, discontinue use and contact a health care professional.

Keep out of the reach of children.

DIRECTIONS:

Shake 10 times before use. Adults and children above 12 years of age: spray 3-4 times under the tongue every 15 minutes, extend interval as symptoms improve or as directed by a health care professional. Children under 12: use half the adult dose.

INACTIVE INGREDIENTS:

Ethanol Alcohol 16%, Glycerin, Purified Water.

QUESTIONS

Mfg. By: OHM PHARMA INC.

Mineral Wells, TX 76067

OTHER SAFETY INFORMATION

Pharmaceutical Grade

Professional Use Only

Product of USA

PURPOSE

Allergy Relief

PACKAGE LABEL

HOMEOPATHIC MEDICINE

NDC: 66096-158-05

ALLERGY RELIEF

Natural - Safe - Effective

No Side Effects

2 fl oz (59 mL) / 16% Alcohol